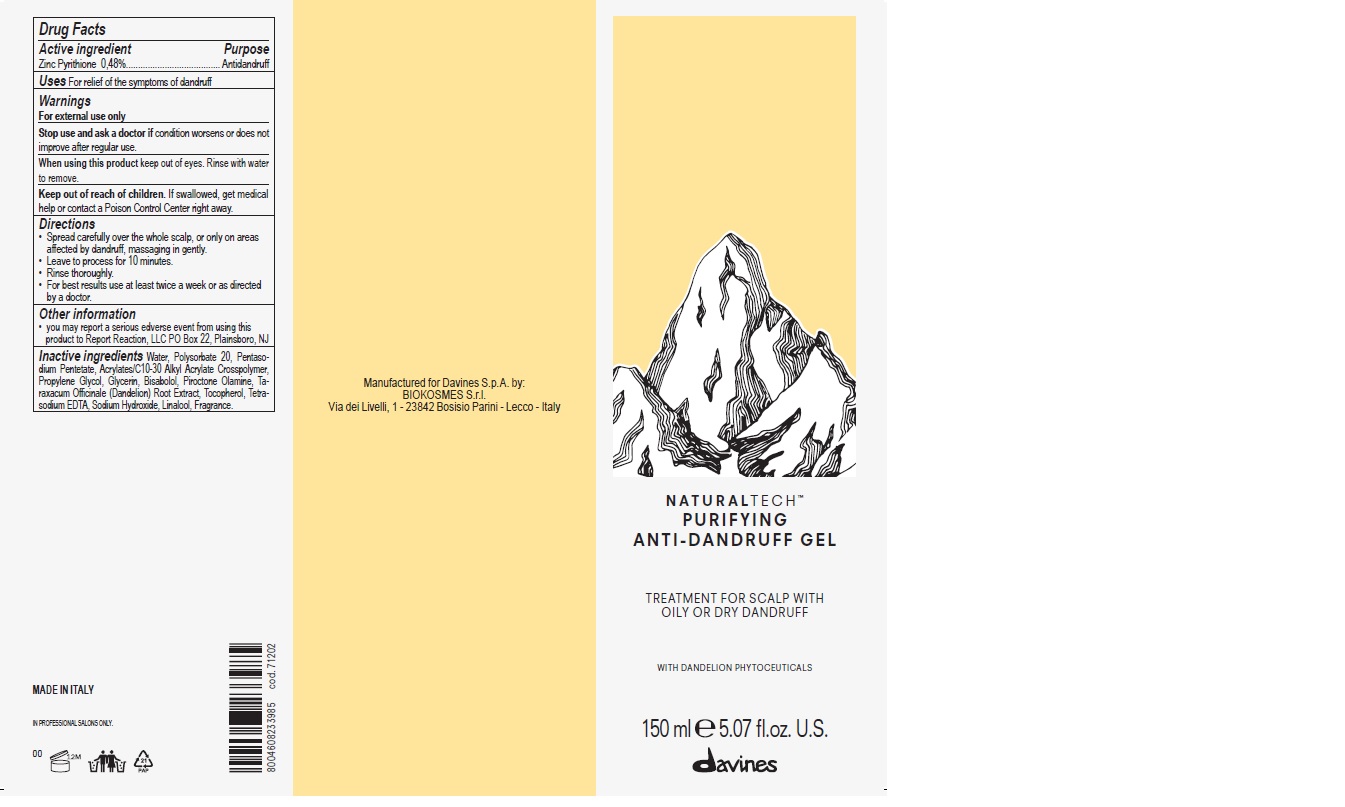 DRUG LABEL: NATURALTECH PURIFYING ANTI-DANDRUFF
NDC: 64724-1017 | Form: GEL
Manufacturer: Davines S.p.A.
Category: otc | Type: HUMAN OTC DRUG LABEL
Date: 20241211

ACTIVE INGREDIENTS: PYRITHIONE ZINC 0.48 g/100 mL
INACTIVE INGREDIENTS: WATER; POLYSORBATE 20; PENTASODIUM PENTETATE; CARBOMER INTERPOLYMER TYPE A (ALLYL SUCROSE CROSSLINKED); PROPYLENE GLYCOL; GLYCERIN; LEVOMENOL; PIROCTONE OLAMINE; TARAXACUM OFFICINALE; TOCOPHEROL; EDETATE SODIUM; SODIUM HYDROXIDE; LINALOOL, (+/-)-

NATURALTECH PURIFYING ANTI-DANDRUFF Gel

Active Ingredient

Zinc Pyrithione 0,48%

Purpose

Antidandruff

Uses

For relief of the symptoms of dandruff

Warnings

For external use only

Stop use and ask a doctor if

condition worsens or does not improve after regular use

When using this product

keep out of eyes. Rinse with water to remove.

Keep out of reach of children

If swallowed, get medical help or contact a Poison Control Center right away

Directions

- Spread carefully over the whole scalp, or only on areas affected by dandruff, massaging in gently.
- Leave to process for 10 minutes.
- Rinse thoroughly.
- For best results use at least twice a week or as directed by a doctor.

Other information

- you may report a serious adverse event from using this product to Report Reaction, LLC PO Box 22, Plainsboro, NJ

Inactive Ingredients

Water, Polysorbate 20, Pentasodium Pentetate, Acrylates/C10-30 Alkyl Acrylate Crosspolymer, Propylene Glycol, Glycerin, Bisabolol, Piroctone Olamine, Taraxacum Officinale (Dandelion) Root Extract, Tocopherol, Tetrasodium EDTA, Sodium Hydroxide, Linalool, Fragrance.

PRINCIPAL DISPLAY PANEL - 150 mL Bottle Carton Label

NATURALTECH™
PURIFYING ANTI-DANDRUFF GEL

TREATMENT FOR SCALP WITH
OILY OR DRY DANDRUFF

WITH DANDELION PHYTOCEUTICALS

150 mL 5.07 Fl. Oz.

davines